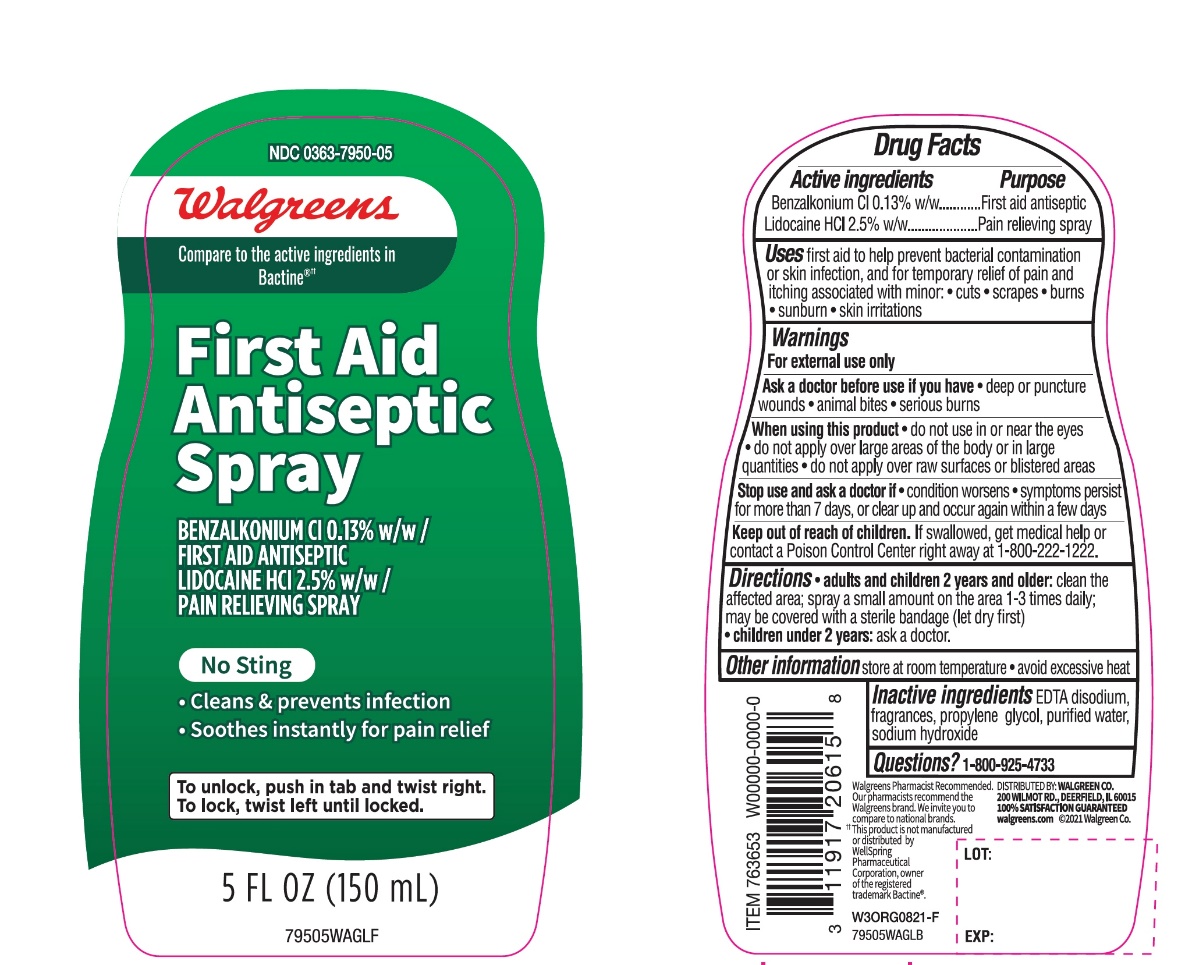 DRUG LABEL: Walgreens
NDC: 0363-7950 | Form: SPRAY
Manufacturer: Walgreens
Category: otc | Type: HUMAN OTC DRUG LABEL
Date: 20251126

ACTIVE INGREDIENTS: BENZALKONIUM CHLORIDE 0.13 g/1 mL; LIDOCAINE HYDROCHLORIDE 25 mg/1 mL
INACTIVE INGREDIENTS: EDETATE DISODIUM ANHYDROUS; PROPYLENE GLYCOL; WATER; PROPYLPARABEN; SODIUM HYDROXIDE

Walgreen First Aid Antiseptic Spray

Active ingredients

Benzalkonium Cl 0.13% w/w

Lidocaine HCI 2.5% w/w

Purpose

First Aid Antiseptic

Pain Relieving Spray

Uses

First aid to help prevent bacterial contamination or skin infection, and for temporary relief of pain and itching associated with minor: cuts, scrapes, burns, sunburn, skin irritations

Warnings

For external use only

Ask a doctor before use if you have

- deep or puncture wounds
- animal bites
- serious burns

When using this product

- do not use in or near the eyes
- do not apply over large area of the body or in large quantities
- do not apply over raw surfaces or blistered areas

Stop use and ask a doctor if

- condition worsens
- symptoms persist for more than 7 days, or clear up and occur again within a few days

Keep out of reach of children

If swallowed get medical help or contact a Poison Control Center right away at 1-800-222-1222

Directions

- adults and children 2 years and older:clean the affected area. spray small amount on the area 1-3 times daily; may be covered with sterile bandage (let dry first)
- children under 2 years:ask a doctor

Other information

- Store at room temperature
- avoid excessive heat

Inactive ingredients

EDTA disodium, fragrance, propylene glycol, purified water, sodium hydroxide.

Principal Display Panel/Package Label

Walgreens

NDC# 0363-7950-05

Compare to the active ingredients in Bactine®††

First Aid

Antiseptic Spray

BENZALKONIUM Cl 0.13%/

FIRST AID ANTISEPTIC

LIDOCAINE HCl 2.5%/

PAIN RELIEVING SPRAY

NO STING

- Cleans & prevents infection
- Soothes instantly for pain relief

To unlock, push in tab and twist right. To lock, twist left until licked

5 FL OZ (150 mL)

DISTRIBUTED BY: WALGREEN CO.,

200 WILMOT RD., DEERFIELD, IL 60015

100% SATISFACTION GUARANTEED

Walgreens.com 2018 ©Walgreen Co.

Walgreens Pharmacist Recommended, Walgreens Pharmacists Survey

††This product is not manufactured or distributed by Well Spring Pharmaceuticals Corporation, owner of the registered trademark Bactine®